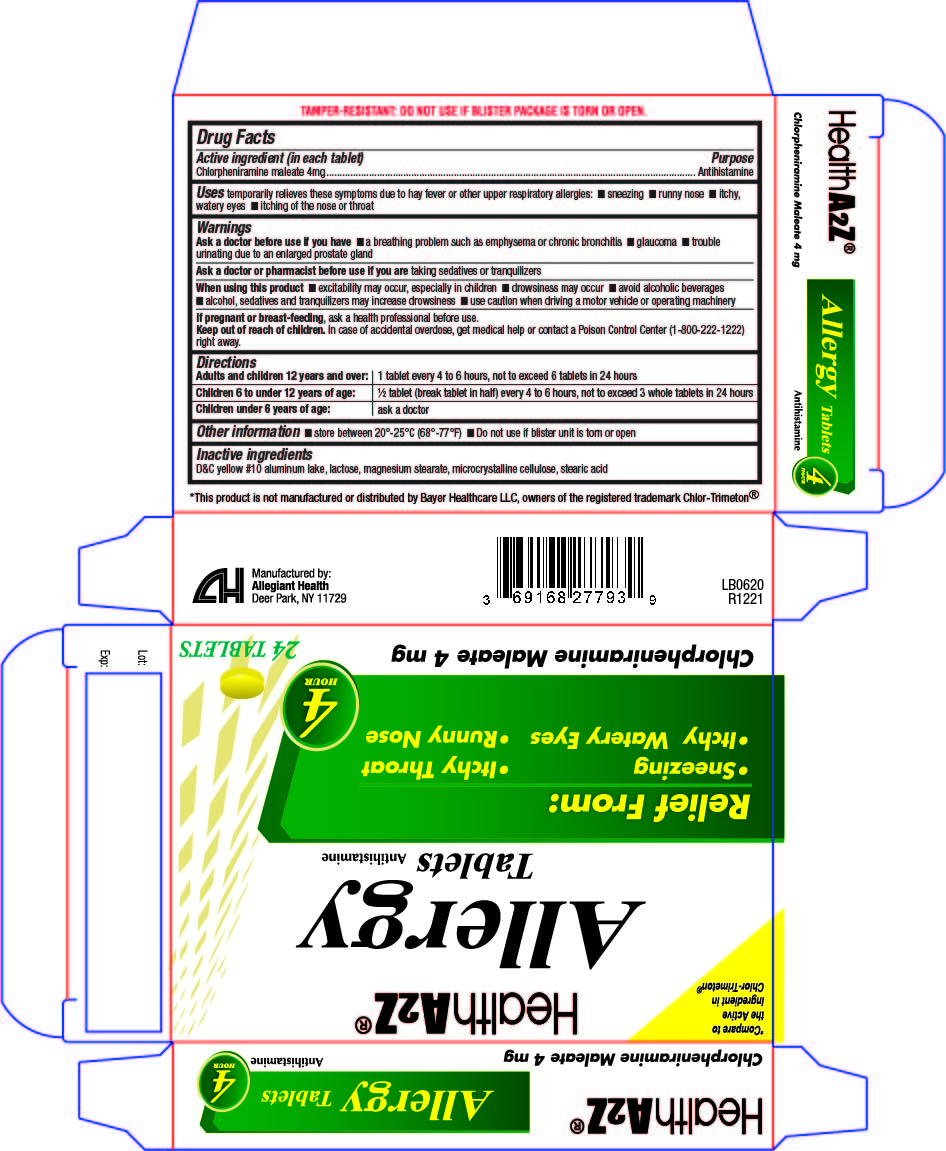 DRUG LABEL: Allergy
NDC: 69168-277 | Form: TABLET
Manufacturer: Allegiant Health
Category: otc | Type: HUMAN OTC DRUG LABEL
Date: 20181226

ACTIVE INGREDIENTS: CHLORPHENIRAMINE MALEATE 4 mg/1 1
INACTIVE INGREDIENTS: D&C YELLOW NO. 10; LACTOSE, UNSPECIFIED FORM; MAGNESIUM STEARATE; CELLULOSE, MICROCRYSTALLINE; STEARIC ACID

Drug Facts

Active ingredient

Chlorpheniramine Maleate 4 mg

Purpose

Antihistamine

Uses

temporarily relieves these symptoms due to hay fever or other upper respiratory allergies:

- sneezing
- runny nose
- itchy, watery eyes
- itching of the nose or throat

Warnings

Ask a doctor before use if you have

- a breathing problem such as emphysema or chronic bronchitis
- glaucoma
- trouble urinating due to an enlarged prostate gland

Ask a doctor or pharmacist before use if you

are taking sedatives or tranquilizers

When using this product

- marked drowsiness may occur
- avoid alcoholic beverages
- alcohol, sedatives, and tranquilizers may increase drowsiness
- be careful when drivinga motor vehicle or operating machinery
- excitability may occur especially in children

If pregnant or breast-feeding, ask a health professional before use.

Keep out of reach of children. In case of accidental overdose, contact a doctor or Poison Control Center immediately

Directions

- take every 4 to 6 hours
- do not take more than 6 doses in 24 hours
- Adults and children 12 years and over: 1 tablet
- Children 6 to under 12 years: 1/2 tablet Children under 6 years: consult a doctor

Inactive Ingredients

D&C yellow #10 aluminum lake, lactose, magnesium stearate, microcrystalline cellulose, stearic acid

Package/Label Principal Display Panel

Allergy